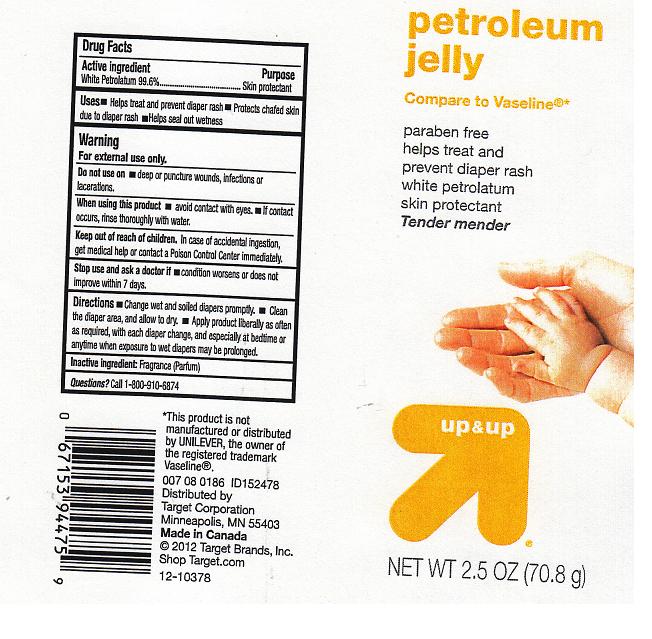 DRUG LABEL: UP AND UP
NDC: 11673-351 | Form: JELLY
Manufacturer: TARGET CORPORATION
Category: otc | Type: HUMAN OTC DRUG LABEL
Date: 20120416

ACTIVE INGREDIENTS: PETROLATUM 99.6 g/100 g
INACTIVE INGREDIENTS: PETROLATUM

DRUG FACTS

ACTIVE INGREDIENT

WHITE PETROLATUM 99.6%

PURPOSE

SKIN PROTECTANT

USES

HELPS TREAT AND PREVENT DIAPER RASH. PROTECTS CHAFED SKIN DUE TO DIAPER RASH. HELPS SEAL OUT WETNESS.

WARNING

FOR EXTERNAL USE ONLY.

DO NOT USE ON

DEEP OR PUNCTURE WOUNDS, INFECTIONS OR LACERATIONS.

WHEN USING THIS PRODUCT

AVOID CONTACT WITH EYES. IF CONTACT OCCURS, RINSE THOROUGHLY WITH WATER.

KEEP OUT OF REACH OF CHILDREN

IN CASE OF ACCIDENTAL INGESTION, GET MEDICAL HELP OR CONTACT A POISON CONTROL CENTER IMMEDIATELY.

STOP USE AND ASK A DOCTOR IF

CONDITION WORSENS OR DOES NOT IMPROVE WITHIN 7 DAYS.

DIRECTIONS

CHANGE WET AND SOILED DIAPERS PROMPTLY. CLEAN THE DIAPER AREA, AND ALLOW TO DRY. APPLY PRODUCT LIBERALLY AS OFTEN AS REQUIRED, WITH EACH DIAPER CHANGE, AND ESPECIALLY AT BEDTIME OR ANYTIME WHEN EXPOSURE TO WET DIAPERS MAY BE PROLONGED.

INACTIVE INGREDIENT:

FRAGRANCE (PARFUM)

QUESTIONS?

CALL 1-800-910-6874